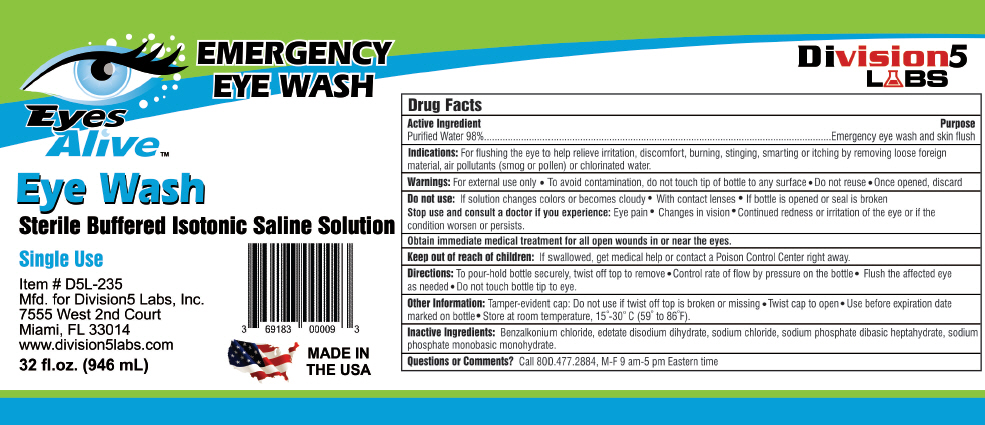 DRUG LABEL: Eyes Alive Eye Wash
NDC: 69183-230 | Form: SOLUTION
Manufacturer: DIVISION 5 LABS, INC.
Category: otc | Type: HUMAN OTC DRUG LABEL
Date: 20191207

ACTIVE INGREDIENTS: Water 980 mg/1 mL
INACTIVE INGREDIENTS: Benzalkonium chloride; edetate disodium; sodium chloride; sodium phosphate, dibasic, heptahydrate; sodium phosphate, monobasic, monohydrate

Eyes Alive™ Eye Wash

Drug Facts

Active Ingredient

Purified Water 98%

Purpose

Emergency eye wash and skin flush

Indications

For flushing the eye to help relieve irritation, discomfort, burning, stinging, smarting or itching by removing loose foreign material, air pollutants (smog or pollen) or chlorinated water.

Warnings

For external use only

- To avoid contamination, do not touch tip of bottle to any surface
- Do not reuse
- Once opened, discard

Do not use

If solution changes colors or becomes cloudy

- With contact lenses
- If bottle is opened or seal is broken

Stop use and consult a doctor if you experience

Eye pain

- Changes in vision
- Continued redness or irritation of the eye or if the condition worsen or persists.

Obtain immediate medical treatment for all open wounds in or near the eyes.

Keep out of reach of children

If swallowed, get medical help or contact a Poison Control Center right away.

Directions

To pour-hold bottle securely, twist off top to remove

- Control rate of flow by pressure on the bottle
- Flush the affected eye as needed
- Do not touch bottle tip to eye.

Other Information

Tamper-evident cap: Do not use if twist off top is broken or missing

- Twist cap to open
- Use before expiration date marked on bottle
- Store at room temperature, 15°-30° C (59° to 86°F).

Inactive Ingredients

Benzalkonium chloride, edetate disodium dihydrate, sodium chloride, sodium phosphate dibasic heptahydrate, sodium phosphate monobasic monohydrate.

Questions or Comments?

Call 800.477.2884, M-F 9 am-5 pm Eastern time

PRINCIPAL DISPLAY PANEL - 946 mL Bottle Label

EMERGENCY
EYE WASH

Eyes
Alive™

Eye Wash
Sterile Buffered Isotonic Saline Solution

Single Use

Item # D5L-235
Mfd. for Division5 Labs, Inc.
7555 West 2nd Court
Miami, FL 33014
www.division5labs.com

32 fl.oz. (946 mL)

MADE IN
THE USA